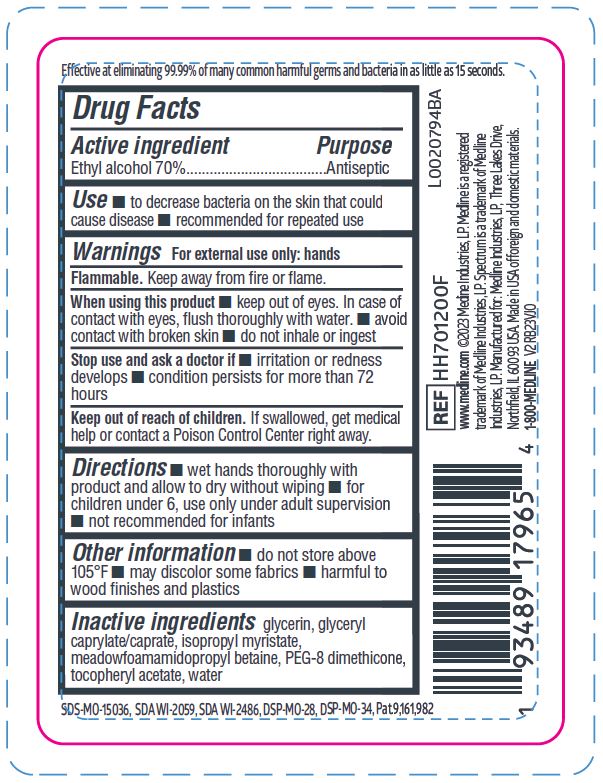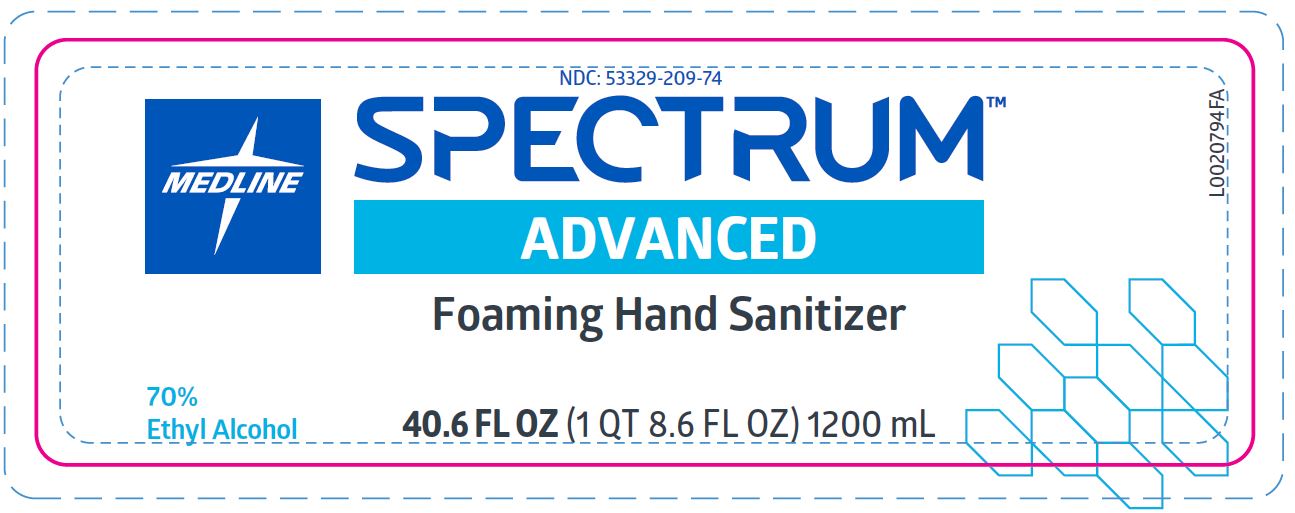 DRUG LABEL: Hand Sanitizer
NDC: 53329-209 | Form: LIQUID
Manufacturer: Medline Industries, LP
Category: otc | Type: HUMAN OTC DRUG LABEL
Date: 20260211

ACTIVE INGREDIENTS: ALCOHOL 0.879 mg/1 mL
INACTIVE INGREDIENTS: PEG-8 DIMETHICONE; MEADOWFOAMAMIDOPROPYL BETAINE; WATER; GLYCERYL CAPRYLATE/CAPRATE; GLYCERIN; .ALPHA.-TOCOPHEROL ACETATE; ISOPROPYL MYRISTATE

209 Advanced Foaming Hand Sanitizer

Active ingredient

Ethyl alcohol 70% v/v

Purpose

Antiseptic

Use

- to decrease bacteria on the skin that could cause disease
- recommended for repeated use

Warnings

For external use only: hands only

Flammable. Keep away from fire or flame.

When using this product

- keep out of eyes. In case of contact with eyes, flush thoroughly with water.
- avoid contact with broken skin
- do not inhale or ingest

Stop use and ask a doctor if

- irritation or redness develops
- condition persists for more than 72 hours

Keep out of reach children

If swallowed, get medical help or contact a Poison Control Center right away.

Directions

- wet hands thoroughly with product and allow to dry without wiping
- for children under 6, use only under adult suervision
- not recommended for infants

Other information

- do not store above 105°F
- may discolor some fabrics
- harmful to wood finishes and plastics

Inactive ingredients

glycerin, glyceryl caprylate/caprate, isopropyl myristate, meadowfoamamidopropyl betaine, PEG-8 dimethicone, tocopheryl acetate, water

Manufacturing Information

Manufactured for:

Medline Industries, LP

Three Lakes Drive, Northfield, IL 60093 USA

Made in USA with US and foreign components

www.medline.com

1-800-MEDLINE

REF: HH701200F

V2 RB23VJO